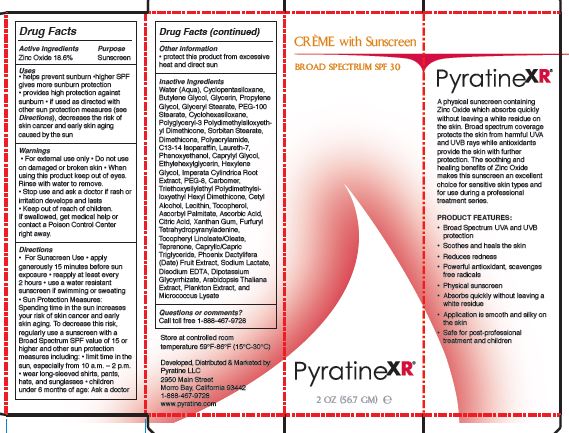 DRUG LABEL: Pyratine XR Creme With Sunscreen Broad Spectrum SPF30
NDC: 62742-4145 | Form: CREAM
Manufacturer: Allure Labs Inc
Category: otc | Type: HUMAN OTC DRUG LABEL
Date: 20171207

ACTIVE INGREDIENTS: ZINC OXIDE 186 mg/1 g
INACTIVE INGREDIENTS: WATER; DIMETHICONE CROSSPOLYMER (450000 MPA.S AT 12% IN CYCLOPENTASILOXANE); BUTYLENE GLYCOL; GLYCERIN; MEDIUM-CHAIN TRIGLYCERIDES; GLYCERYL STEARATE SE; PEG-100 STEARATE; POLYGLYCERYL-3 POLYDIMETHYLSILOXYETHYL DIMETHICONE (4000 MPA.S); CYCLOMETHICONE 6; SORBITAN MONOSTEARATE; POLYACRYLAMIDE (10000 MW); C13-14 ISOPARAFFIN; LAURETH-7; PHENOXYETHANOL; CAPRYLYL GLYCOL; ETHYLHEXYLGLYCERIN; HEXYLENE GLYCOL; IMPERATA CYLINDRICA ROOT; POLYETHYLENE GLYCOL 400; CARBOMER 1342; CETYL ALCOHOL; LECITHIN, SOYBEAN; TOCOPHEROL; ASCORBYL PALMITATE; ASCORBIC ACID; CITRIC ACID MONOHYDRATE; XANTHAN GUM; POLYESTER-7; NEOPENTYL GLYCOL DIHEPTANOATE; .ALPHA.-TOCOPHEROL LINOLEATE, D-; TEPRENONE; DATE; POLYGONUM AVICULARE TOP; SODIUM LACTATE; EDETATE DISODIUM ANHYDROUS; GLYCYRRHIZINATE DIPOTASSIUM; ARABIDOPSIS THALIANA; MICROCOCCUS LUTEUS; TRIETHOXYCAPRYLYLSILANE

Drug Facts

Active Ingredient: Zinc oxide - 18.6%

Purpose: Sunscreen

Uses:

- Help prevent sunburn. Higher SPF gives more sunburn protection. Provide high protection against sunburn. If used as directed with other sun protection measures (see Directions), decreases the risk of skin cancer and early skin aging caused by the sun.

WARNINGS

Warnings: For external use only. Do not use on damaged or broken skin.

When using this product keep out of eyes. Rinse with water to remove.

Stop use and ask a doctor if rash or irritation developes and lasts.

Keep out of reach of children. If swallowed, get medical help or contact a Poison Cpntrol center right away.

Directions:

- For sunscreen use. Apply generously 15 minutes before sun exposure. Reapply at least every 2 hours. Use a water resistant sunscreen if swimming or sweating.
- Sun protection measures: Spending time in the sun increases your risk of skin cancer and early skin aging. To decrease this risk, regularly use a sunscreen with a Broad Spectrum SPF value of 15 or higher and other protection measures including: limit time in the sun, especially from 10 am - 2 pm. Wear long-sleeved shirts, pants, hats, and sunglasses. Children under 6 months of age: Ask a doctor.

OTHER SAFETY INFORMATION

protect this product from excessive heat and direct sun.

QUESTIONS

Call toll free 1-888-467-9728

STORAGE AND HANDLING

Store at controlled room temperature 59 F - 89 F (15 C - 30 C).

INACTIVE INGREDIENT

Inactive Ingredients: Water (Aqua), Cyclopentasiloxane, Butylene glycol, glycerin, Propylene Glycol, Caprylic/Capric triglyceride, Glycerin Stearate, PEG-100 Stearate, Polyglyceryl-3 Polymethylsiloxyeethyl Dimethicon, Cyclohexasiloxane, Sorbitan Stearate, Dimethicone, Polyacrylamide, C13-14 Isoparaffin, Laureth-7,phenoxyethanol, Caprylyl Glycol, Ethylhexyglycerin, Hexylene glycol, Imperata Cylindrica Root Extract, PEG-8, Carbomer, triethoxysilylethyl Polydimethylsiloxyethyl Hexyl Dimethicone, Cetyl Alcohol, Lecithin, Tocopherol, Ascorbyl Palmitate, Ascorbic Acid, Citric Acid, Xanthan gum, Furfuryl Tetrahydropyranyladinine, tocopherol Linoleate/Oleate, Teprenone, Phoenix Dactylifera (Date) Fruit Extract, Sodium Lactate, Disodium EDTA, Dipotassium Glycyrrhizate, Arabidopsis Thaliana Extract, Plankton Extract and Micrococcus Lysate.

PACKAGE LABEL

Developed, Distributed and Marketed by:

Pyratine LLC

2950 Main Street

Morro Bay, CA 93442

1-888-467-9728

www.pyratine.com